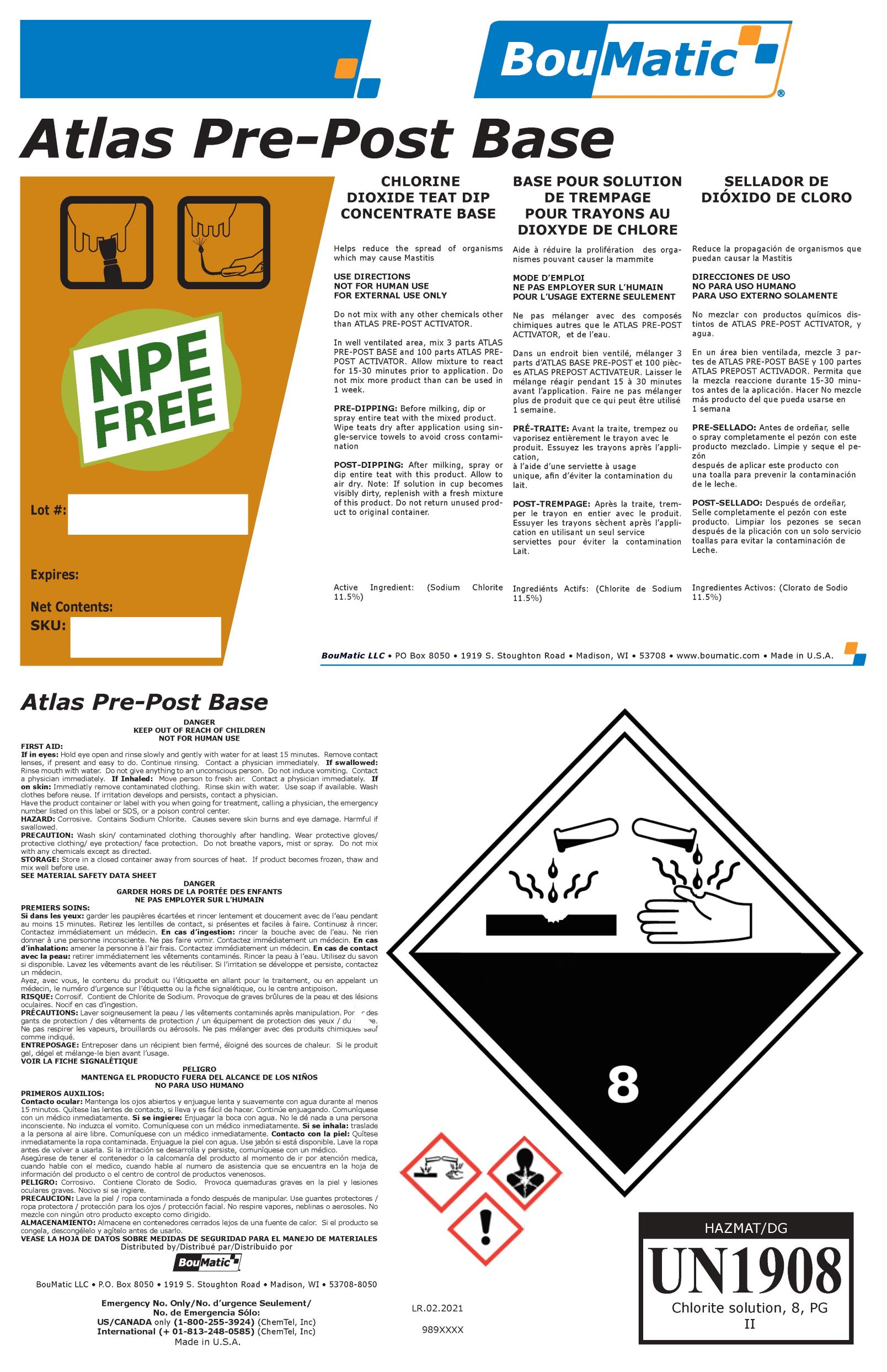 DRUG LABEL: Atlas PrePost Base
NDC: 48106-2033 | Form: LIQUID
Manufacturer: BOUMATIC, LLC
Category: animal | Type: OTC ANIMAL DRUG LABEL
Date: 20210311

ACTIVE INGREDIENTS: SODIUM CHLORITE 115200 [ppm]/1 g

Atlas PrePost Base

Claim of effectiveness.

Helps reduce the spread of organisms
which may cause Mastitis

Use Directions

In well ventilated area, mix 3 parts ATLAS
PRE-POST BASE and 100 parts ATLAS PREPOST
ACTIVATOR. Allow mixture to react
for 15-30 minutes prior to application. Do
not mix more product than can be used in
1 week.
PRE-DIPPING: Before milking, dip or
spray entire teat with the mixed product.
Wipe teats dry after application using single-
service towels to avoid cross contamination
POST-DIPPING: After milking, spray or
dip entire teat with this product. Allow to
air dry. Note: If solution in cup becomes
visibly dirty, replenish with a fresh mixture
of this product. Do not return unused product
to original container.

First Aid

If in eyes: Hold eye open and rinse slowly and gently with water for at least 15 minutes. Remove contact
lenses, if present and easy to do. Continue rinsing. Contact a physician immediately. If swallowed:
Rinse mouth with water. Do not give anything to an unconscious person. Do not induce vomiting. Contact
a physician immediately. If Inhaled: Move person to fresh air. Contact a physician immediately. If
on skin: Immediatly remove contaminated clothing. Rinse skin with water. Use soap if available. Wash
clothes before reuse. If irritation develops and persists, contact a physician.
Have the product container or label with you when going for treatment, calling a physician, the emergency
number listed on this label or SDS, or a poison control center.
HAZARD: Corrosive. Contains Sodium Chlorite. Causes severe skin burns and eye damage. Harmful if
swallowed.

Precautions & Hazards

NOT FOR HUMAN USE
FOR EXTERNAL USE ONLY
Do not mix with any other chemicals other
than ATLAS PRE-POST ACTIVATOR.

PRECAUTION: Wash skin/ contaminated clothing thoroughly after handling. Wear protective gloves/
protective clothing/ eye protection/ face protection. Do not breathe vapors, mist or spray. Do not mix
with any chemicals except as directed.

General Storage

Store in a closed container away from sources of heat. If product becomes frozen, thaw and
mix well before use.

Claim of effectiveness.Package Label AtlasPrePostBase.jpg

Helps reduce the spread of organisms
which may cause Mastitis

Package Label AtlasPrePostBase.jpg